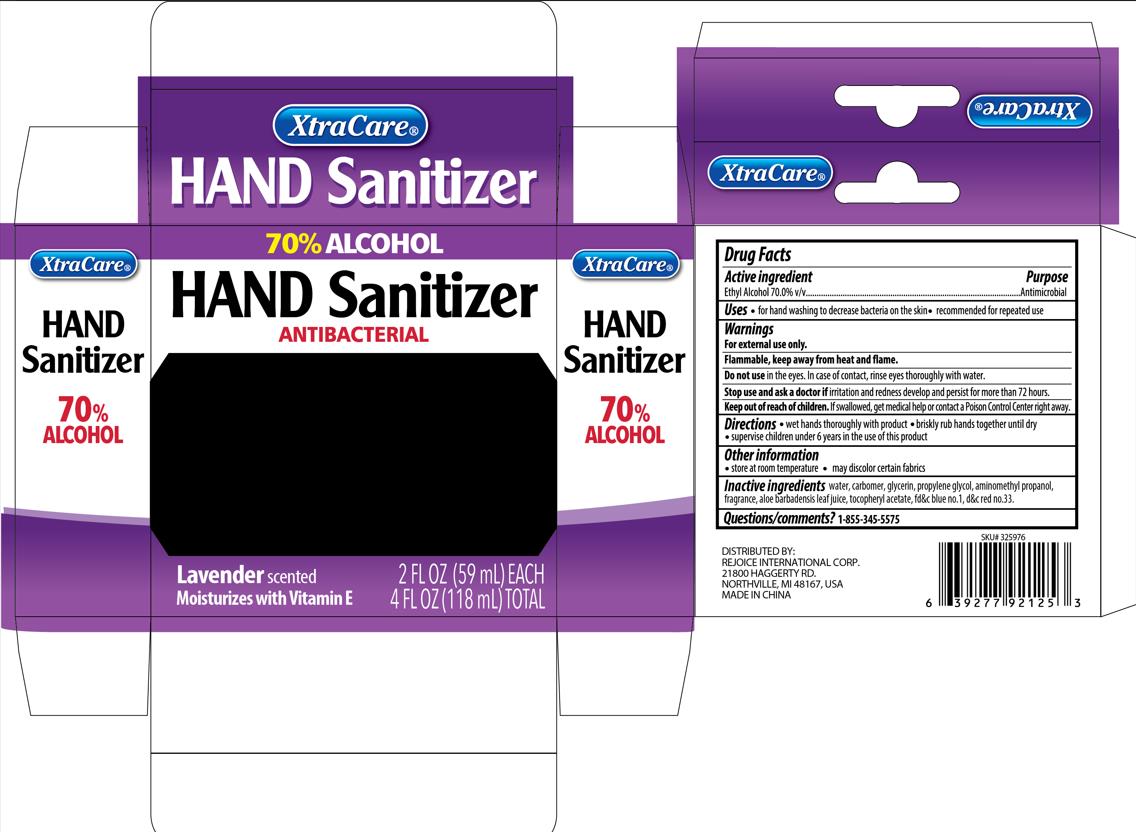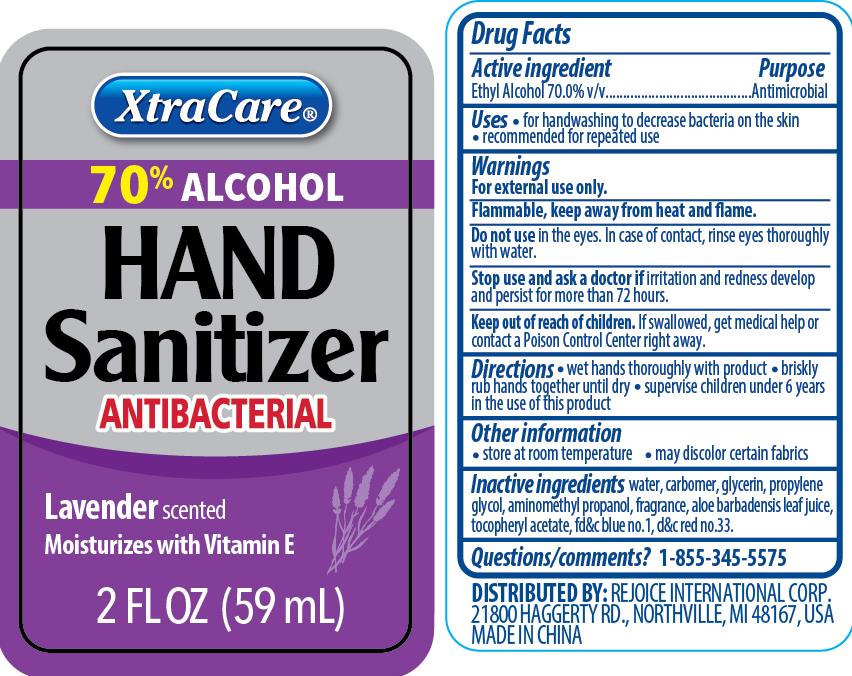 DRUG LABEL: Hand sanitizer 2oz 2pk lavender
NDC: 75742-025 | Form: GEL
Manufacturer: Zhejiang Guoyao Jingyue Aerosol Co., Ltd.
Category: otc | Type: HUMAN OTC DRUG LABEL
Date: 20260105

ACTIVE INGREDIENTS: ALCOHOL 70 mL/100 mL
INACTIVE INGREDIENTS: D&C RED NO. 33; FD&C BLUE NO. 1; WATER; .ALPHA.-TOCOPHEROL ACETATE; GLYCERIN; PROPYLENE GLYCOL; AMINOMETHYLPROPANOL; ALOE VERA LEAF; CARBOMER HOMOPOLYMER, UNSPECIFIED TYPE

Active ingredient

Ethyl Alcohol 70% V/V

Purpose

Antimicrobial

Uses

- for handwashing to decrease bacteria on the skin
- recommended for repeated use

Warnings

For external use only

Flammable, keep away from heat and flame

Do not use in the eyes. In case of contact, rinse eyes thoroughly with water.

Stop use and ask a doctor if irritation and redness develop and persist for more than 72 hours.

Keep out of reach of children

If swallowed , get medical help or contact a Poison Control Center right away.

Directions

- wet hands thoroughly with product
- briskly rub hands together until dry
- supervise children under 6 years in the use of this product

Other inofrmation

- store at room temperature
- may discolor certain fabrics

Inactive ingredients

water

carbomer

glycerin

propylene glycol

aminomethyl propanol

fragrance

aloe barbadensis leaf juice

tocopheryl acetate

fd&c blue no.1

d&c red no.33